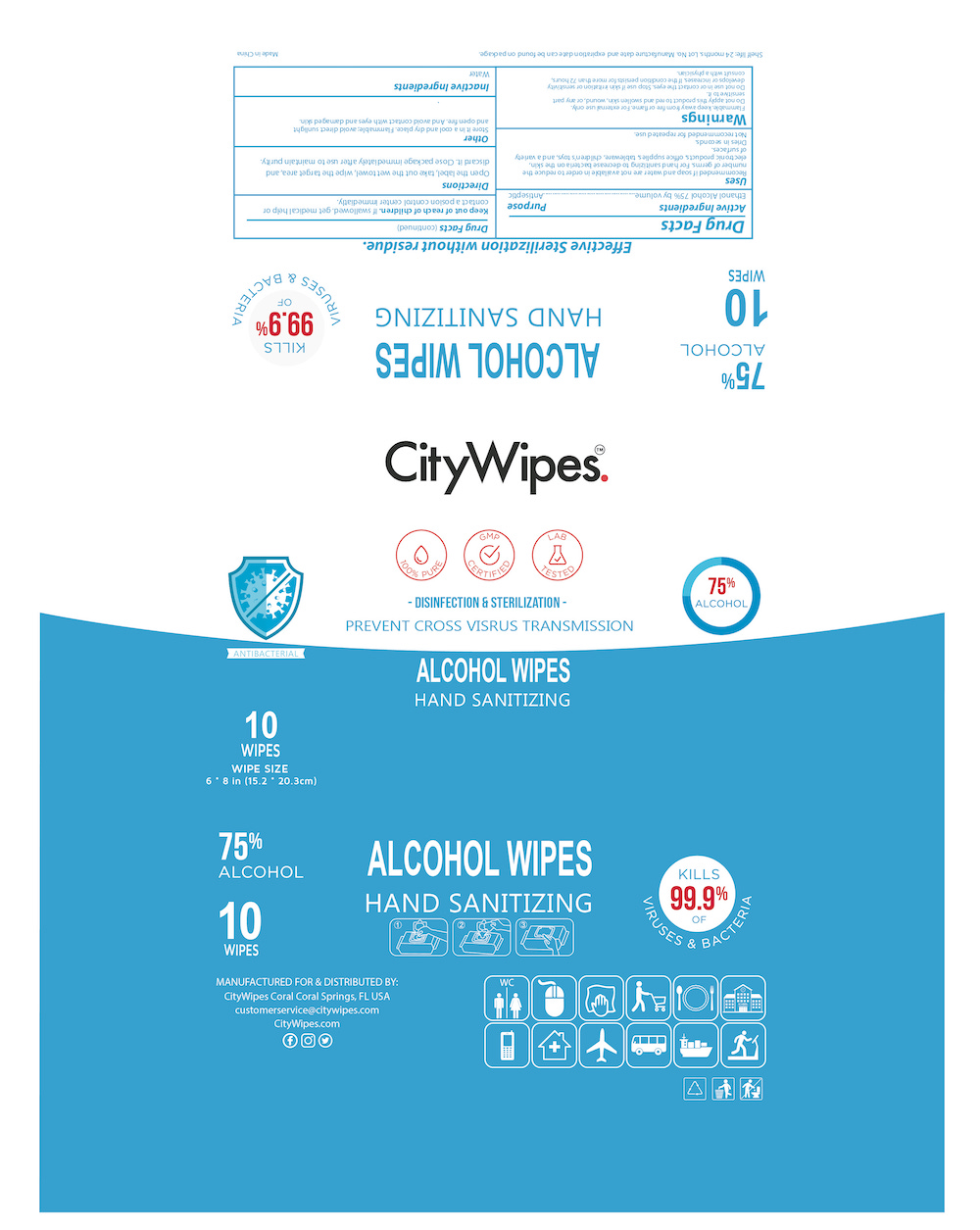 DRUG LABEL: CITYWIPES 75% ALCOHOL WIPES
NDC: 79935-001 | Form: PATCH
Manufacturer: NIKIA MEDIA, INC.
Category: otc | Type: HUMAN OTC DRUG LABEL
Date: 20200721

ACTIVE INGREDIENTS: ALCOHOL 75 U/100 U
INACTIVE INGREDIENTS: WATER

This is a hand sanitizer manufactured according to the Temporary Policy for Preparation of Certain Alcohol-Based Hand Sanitizer Products During the Public Health Emergency (CoViD-19); Guidance for Industry.

The hand sanitizer is manufactured using only the following United States Pharmacopoeia (USP) grade ingredients in the preparation of the product (percentage in final product formulation) consistent with World Health Organization (WHO) recommendations:

1. Alcohol (ethanol) (USP or Food Chemical Codex (FCC) grade) (75%, volume/volume (v/v)) in an aqueous solution denatured according to Alcohol and Tobacco Tax and Trade Bureau regulations in 27 CFR part 20.
2. Sterile distilled water or boiled cold water.

The firm does not add other active or inactive ingredients. Different or additional ingredients may impact the quality and potency of the product.

Active Ingredient(s)

Ethanol Alcohol, 75% v/v, antiseptic

Purpose

Daily cleaning of items and Antimicrobial

Use

This product is used to wipe hands, faces, skins, etc. It can be used on hands, skin, electronic products, office supplies, tableware, children's toys, and a variety of surfaces. Open the label, take out the wet towel, wipe the target area, and discard it in a trash receptacle. Close package immediately after use to maintain purity.

Warnings

Do not apply this product to red and swollen skin, wound, or any part sensitive to it. Keep this product out of children’s reach. If swallowed, get medical help or contact a Poison Control Center immediately. For external use only. Avoid contact with eyes & wounded skin. Discontinue use if irritation and redness develop. If the condition persists for more than 72 hours, consult a physician.

Store it in a cool and dry place. Flammable; avoid direct sunlight and open fire. And avoid contact with eyes and damaged skin.

Do not use

- in children less than 2 months of age
- on open skin wounds

WHEN USING

This product is used to wipe hands, skins, electronic products, office supplies, tableware, children's toys, and a variety of surfaces. When using this product keep out of eyes, ears, and mouth. In case of contact with eyes, rinse eyes thoroughly with water.

Stop use and ask a doctor if irritation or rash occurs. These may be signs of a serious condition.

Keep out of reach of children. If swallowed, get medical help or contact a Poison Control Center right away.

Directions

Use it as needed, after following the usage instructions. For external use only.

Other information

- Store between 15-30C (59-86F)
- Avoid freezing and excessive heat above 40C (104F)

Inactive ingredients

Water

Package Label - Principal Display Panel

010 mL NDC: 79935-001-10